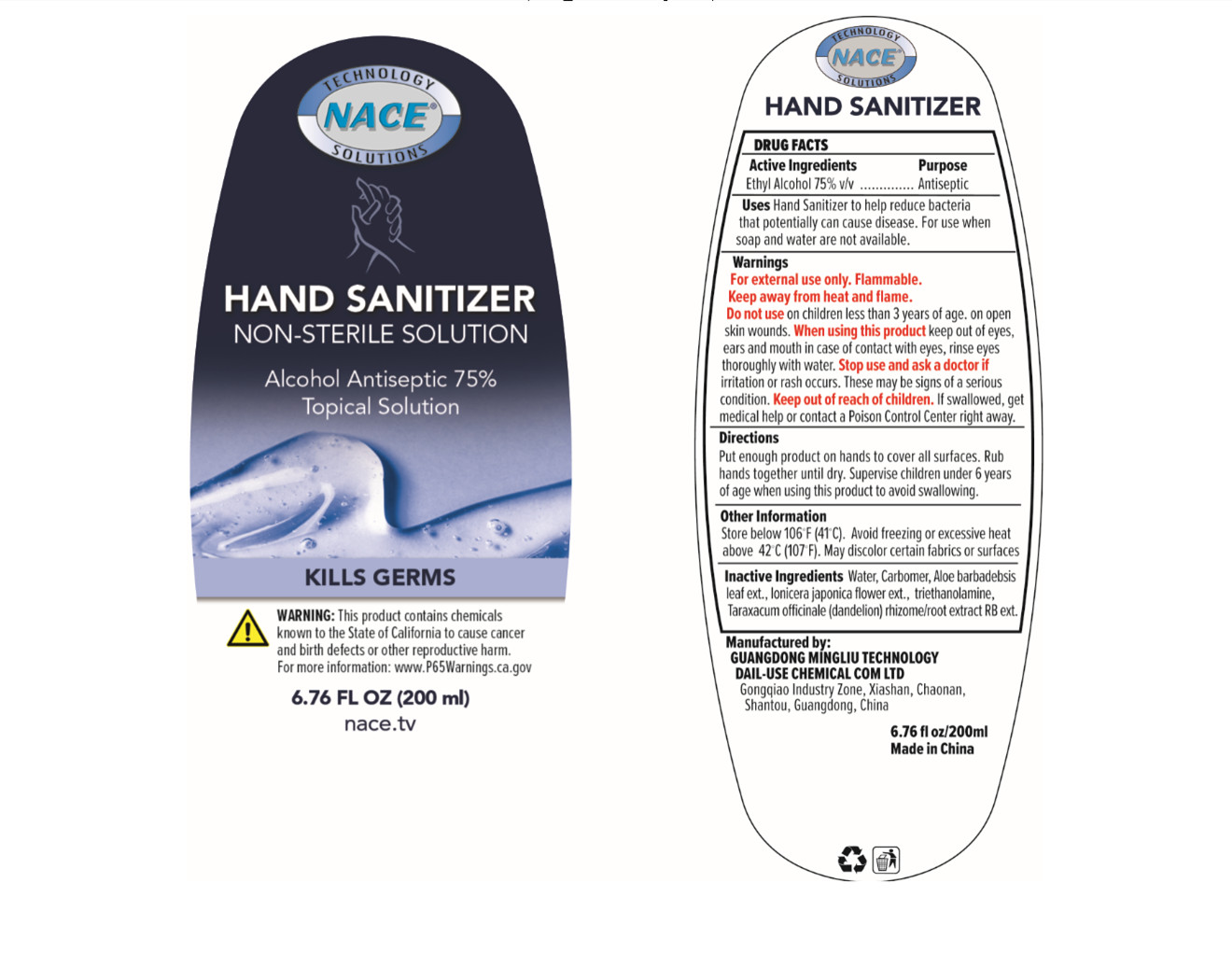 DRUG LABEL: Hand Sanitizer
NDC: 75209-010 | Form: GEL
Manufacturer: GUANGDONG MINGLIU TECHNOLOGY DAIL-USE CHEMICAL CO., LTD.
Category: otc | Type: HUMAN OTC DRUG LABEL
Date: 20200621

ACTIVE INGREDIENTS: ALCOHOL 75 mL/100 mL
INACTIVE INGREDIENTS: CARBOMER 934; LONICERA JAPONICA FLOWER; WATER; TROLAMINE; ALOE VERA LEAF; TARAXACUM OFFICINALE

Hand Sanitizer

Active Ingredient(s)

Active Ingredients Purpose
Ethyl Alcohol 75% v/v .............. Antiseptic

Purpose

Antiseptic

Use

Hand Sanitizer to help reduce bacteria
that potentially can cause disease. For use when
soap and water are not available.

Warnings

For external use only. Flammable.
Keep away from heat and flame.
Do not use on children less than 3 years of age. on open skin wounds. When using this product keep out of eyes,
ears and mouth in case of contact with eyes, rinse eyes thoroughly with water. Stop use and ask a doctor if
irritation or rash occurs. These may be signs of a serious condition. Keep out of reach of children. If swallowed, get
medical help or contact a Poison Control Center right away

Do not use on children less than 3 years of age. on open
skin wounds.

When using this product keep out of eyes, ears and mouth in case of contact with eyes, rinse eyes
thoroughly with water.

Stop use and ask a doctor if irritation or rash occurs. These may be signs of a serious condition.

Keep out of reach of children. If swallowed, get medical help or contact a Poison Control Center right away

Directions

Put enough product on hands to cover all surfaces. Rub hands together until dry. Supervise children under 6 years
of age when using this product to avoid swallowing.

Other information

Store below 106◦F (41◦C). Avoid freezing or excessive heat
above 42◦C (107◦F). May discolor certain fabrics or surfaces

Inactive ingredients

Water, Carbomer, Aloe barbadebsis
leaf ext., Ionicera japonica flower ext., triethanolamine,
Taraxacum officinale (dandelion) rhizome/root extract RB ext.